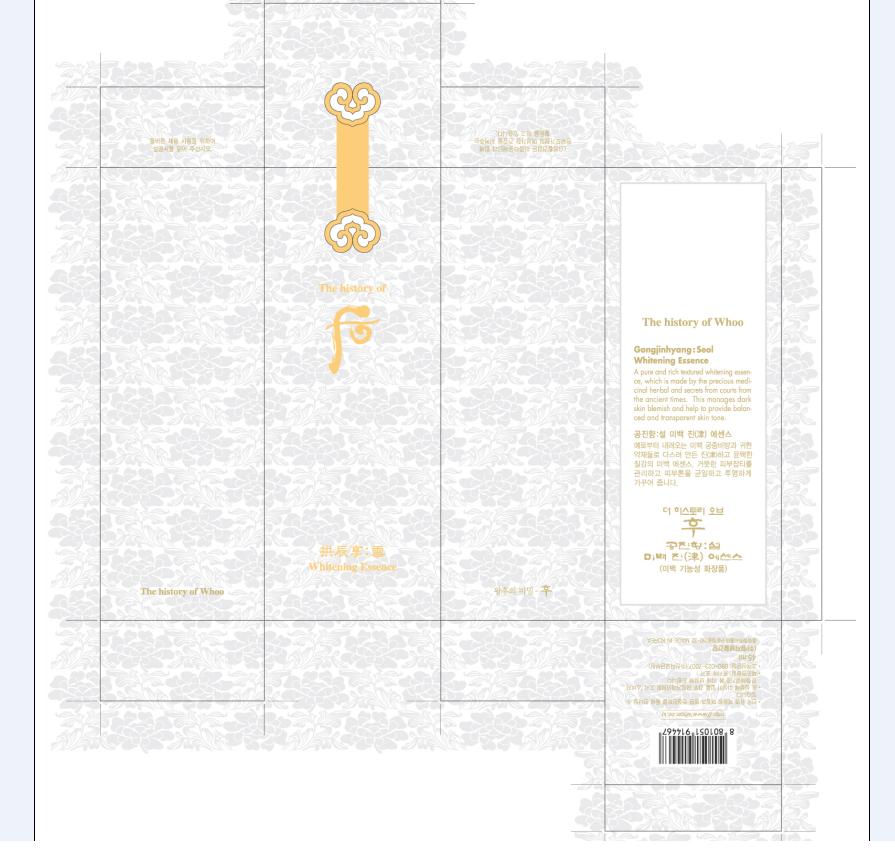 DRUG LABEL: Whoo Gongjinhyang Seol Whitening Jin Essence
NDC: 53208-427 | Form: CREAM
Manufacturer: LG Household and Healthcare, Inc.
Category: otc | Type: HUMAN OTC DRUG LABEL
Date: 20100601

ACTIVE INGREDIENTS: DIOSMETIN 0.055 mL/100 mL
INACTIVE INGREDIENTS: WATER; DIPROPYLENE GLYCOL; GLYCERIN; BUTYLENE GLYCOL; 2-ETHYLHEXANOIC ACID; PANTHENOL; DIMETHICONE; POLYSORBATE 60; GLYCERYL MONOSTEARATE; BETAINE; TROLAMINE; METHYLPARABEN; DIPROPYLENE GLYCOL; CARBOMER 934; PROPYLPARABEN; EDETATE TRISODIUM

Drug Facts

ACTIVE INGREDIENT

DIOSMETIN 0.055ml/100ml

WARNINGS AND PRECAUTIONS

For external use only

Keep out of reach of children. Is swallowed, get medical help or contact a Poison Control Center right away.

WHEN USING

Keep out of eyes. Rinse with water to remove.

Stop use if a rash or irritation develops and lasts.

PACKAGE LABEL

The History of Whoo
Whitening Essence